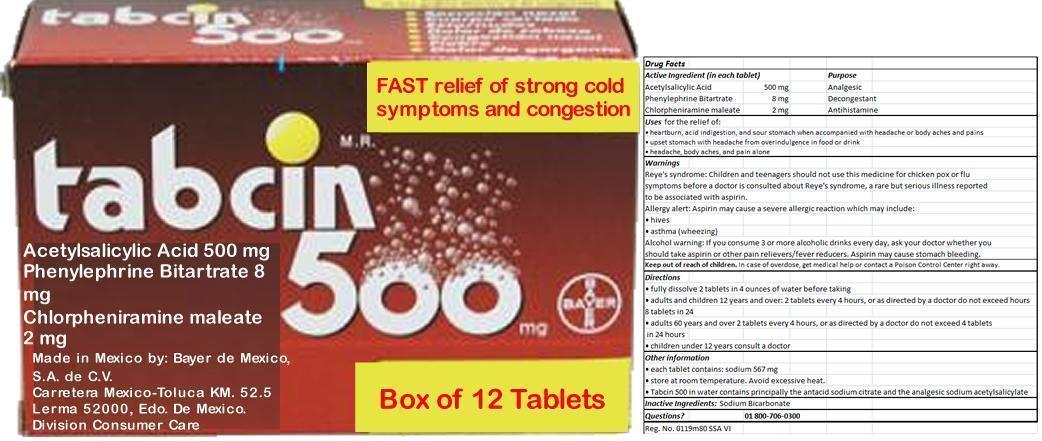 DRUG LABEL: TABCIN
NDC: 53666-408 | Form: TABLET, EFFERVESCENT
Manufacturer: Salimex, S.A.
Category: otc | Type: HUMAN OTC DRUG LABEL
Date: 20130912

ACTIVE INGREDIENTS: ASPIRIN 500 mg/1 1; Phenylephrine Bitartrate 8 mg/1 1; Chlorpheniramine maleate 2 mg/1 1
INACTIVE INGREDIENTS: SODIUM BICARBONATE

TABCIN 500

Active Ingredients (in each tablet)

Acetylsalicylic Acid 500 mg
Phenylephrine Bitartrate 8 mg
Chlorpheniramine maleate 2 mg

Purpose

Acetylsalicylic Acid 500 mg Analgesic
Phenylephrine Bitartrate 8 mg Decongestant
Chlorpheniramine maleate 2 mg Antihistamine

Keep out of reach of children

In case of overdose, get medical help or contact a Poison Control Center right away.

Uses for the relief of:

- heartburn, acid indigestion, and sour stomach when accompanied with headache or body aches and pains
- upset stomach with headache from overindulgence in food or drink
- headache, body aches, and pain alone

Warnings

Reye's syndrome: Children and teenagers should not use this medicine for chicken pox or flu symptoms before a doctor is consulted about Reye's syndrome, a rare but serious illness reported to be associated with aspirin.

Allergy alert: Aspirin may cause a severe allergic reaction which may include:

- hives
- asthma (wheezing)

Alcohol warning: If you consume 3 or more alcoholic drinks every day, ask your doctor whether you should take aspirin or other pain relievers/fever reducers. Aspirin may cause stomach bleeding.

Directions

- fully dissolve 2 tablets in 4 ounces of water before taking
- adults and children 12 years and over: 2 tablets every 4 hours, or as directed by a doctor do not exceed 8 tablets in 24 hours
- adults 60 years and over 2 tablets every 4 hours, or as directed by a doctor do not exceed 4 tablets in 24 hours
- children under 12 years consult a doctor

Other information

- each tablet contains: sodium 567 mg
- store at room temperature. Avoid excessive heat.
- Tabcin 500 in water contains principally the antacid sodium citrate and the analgesic sodium acetylsalicylate

Inactive ingredients

Sodium Bicarbonate

Questions or comments?

01 800-706-0300